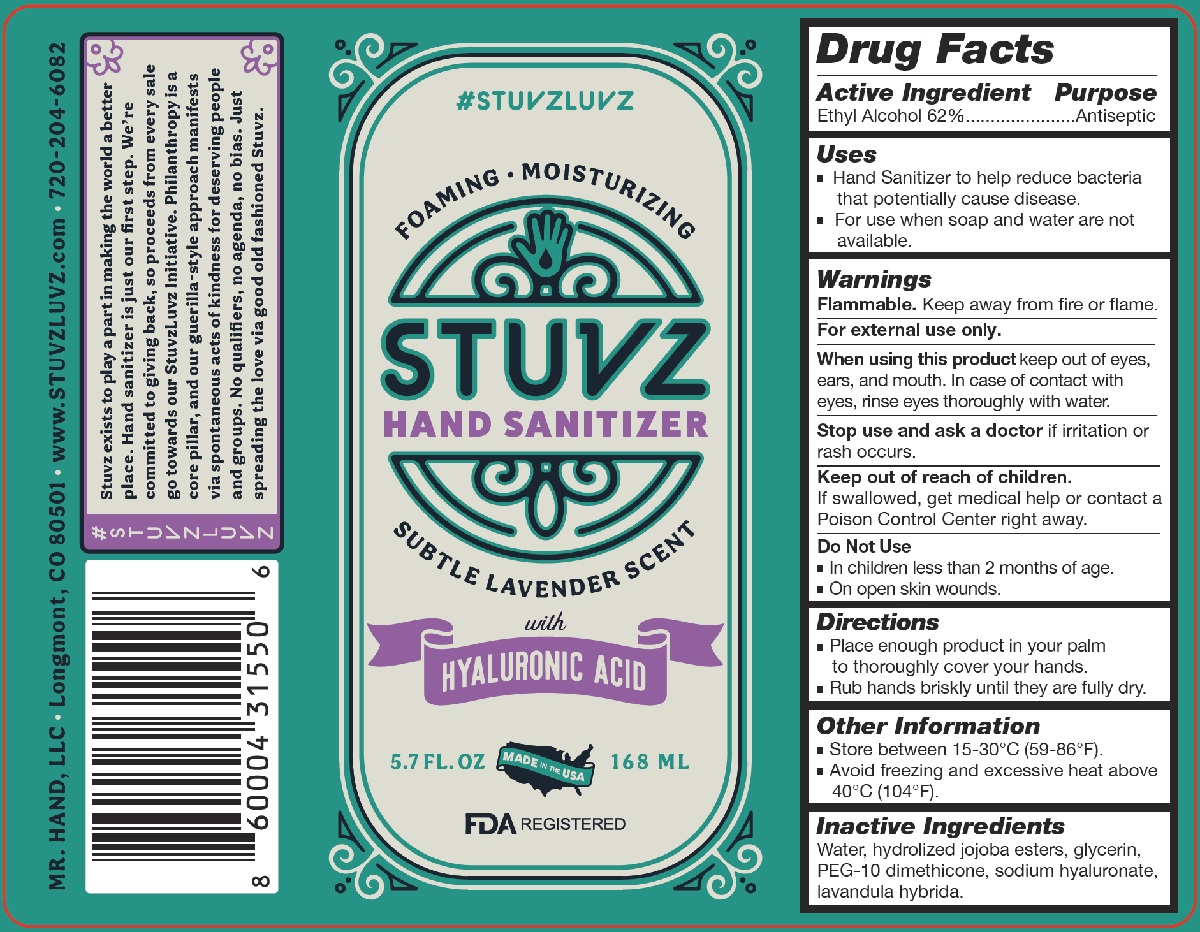 DRUG LABEL: Stuvz Hand Sanitizer
NDC: 79283-002 | Form: LIQUID
Manufacturer: MR. HAND, LLC
Category: otc | Type: HUMAN OTC DRUG LABEL
Date: 20201027

ACTIVE INGREDIENTS: ALCOHOL 0.62 mL/1 mL
INACTIVE INGREDIENTS: GLYCERIN; HYALURONATE SODIUM; WATER; POLYETHYLENE GLYCOL 500; DIMETHICONE; JOJOBA OIL, RANDOMIZED; LAVANDIN OIL

Stuvz Hand Sanitizer

Active Ingredient

Ethyl Alcohol 62%

Purpose

Antiseptic

Uses

- Hand Sanitizer to help reduce bacteria that potentially cause disease.
- For use when soap and water are not available.

Warnings

Flammable. Keep away from fire or flame.

For external use only.

When using this product keep out of eyes, ears, and mouth. In case of contact with eyes, rinse eyes thoroughly with water.

Stop use and ask a doctor if irritation or rash occurs.

Keep out of reach of children.

If swallowed, get medical help or contact a Poison Control Center right away.

Do Not Use

- In children less than 2 months of age.
- On open skin wounds

Directions

- Place enough product in your palm to thoroughly cover your hands.
- Rub hands briskly until they are fully dry.

Other Information

- Store between 15-30°C (59-86°F).
- Avoid freezing and excessive heat above 40°C (104°F).

Inactive Ingredients

Water, hydrolized jojoba esters, glycerin, PEG-10 dimethicone, sodium hyaluronate, lavandula hybrida.

PACKAGE LABEL

Stuvz Hand Sanitizer

With Hyaluronic Acid

5.7 FL. OZ/168 ML